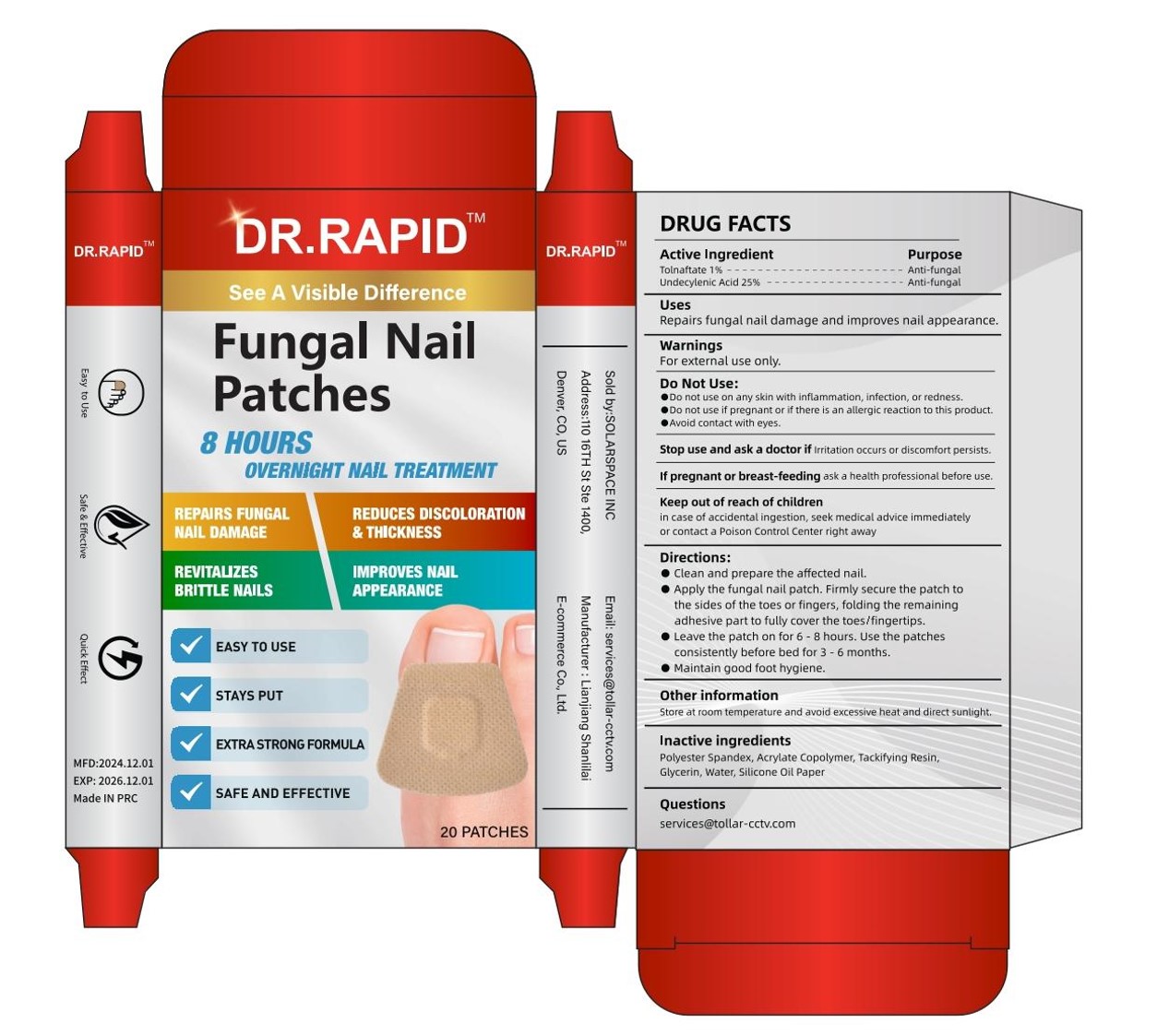 DRUG LABEL: Fungal Nail Patches
NDC: 85038-005 | Form: PATCH
Manufacturer: Lianjiang Shanlilai E-commerce Co., Ltd.
Category: otc | Type: HUMAN OTC DRUG LABEL
Date: 20241219

ACTIVE INGREDIENTS: UNDECYLENIC ACID 25 g/100 1; TOLNAFTATE 1 g/100 1
INACTIVE INGREDIENTS: ACRYLIC ACID/SODIUM ACRYLATE COPOLYMER (1:1; 600 MPA.S AT 0.2%); GLYCERIN; WATER

Fungal Nail Patches

Fungal Nail Patches

ACTIVE INGREDIENT

TOLNAFTATE 1%
UNDECYLENIC ACID 25%

PURPOSE

Anti-fungal

INDICATIONS AND USAGE

Repairs fungal nail damage and improves nail appearance.

WARNINGS

For external use only.

Do not use on any skin with inflammation,infectlon, or redness.

Do not use if preqnant or if there is an allergic reaction to this product

Avoid contact with eyes.

Stop use and ask a doctor if lrritation occurs or discomfort persists

KEEP OUT OF REACH OF CHILDREN

in case of accidental ingestion, seek medical advice immediatelyor contact a Poison Control Center right away

DOSAGE AND ADMINISTRATION

Clean and prepare the affected nail.
Apply the fungal nail patch. Firmly secure the patch tothe sides of the toes or fingers, folding the remainingadhesive part to fully cover the toesffingertips.

Leave the patch on for 6 -8 hours. Use the patchesconsistently before bed for 3 -é months.

Maintain good foot hygiene.

STORAGE AND HANDLING

Store at room temperature and avoid excessive heat and direct sunlight.

INACTIVE INGREDIENT

Polyester Spandex
Acrylate Copolymer
Tackifying Resin
Glycerin
Water
Silicone Oil Paper